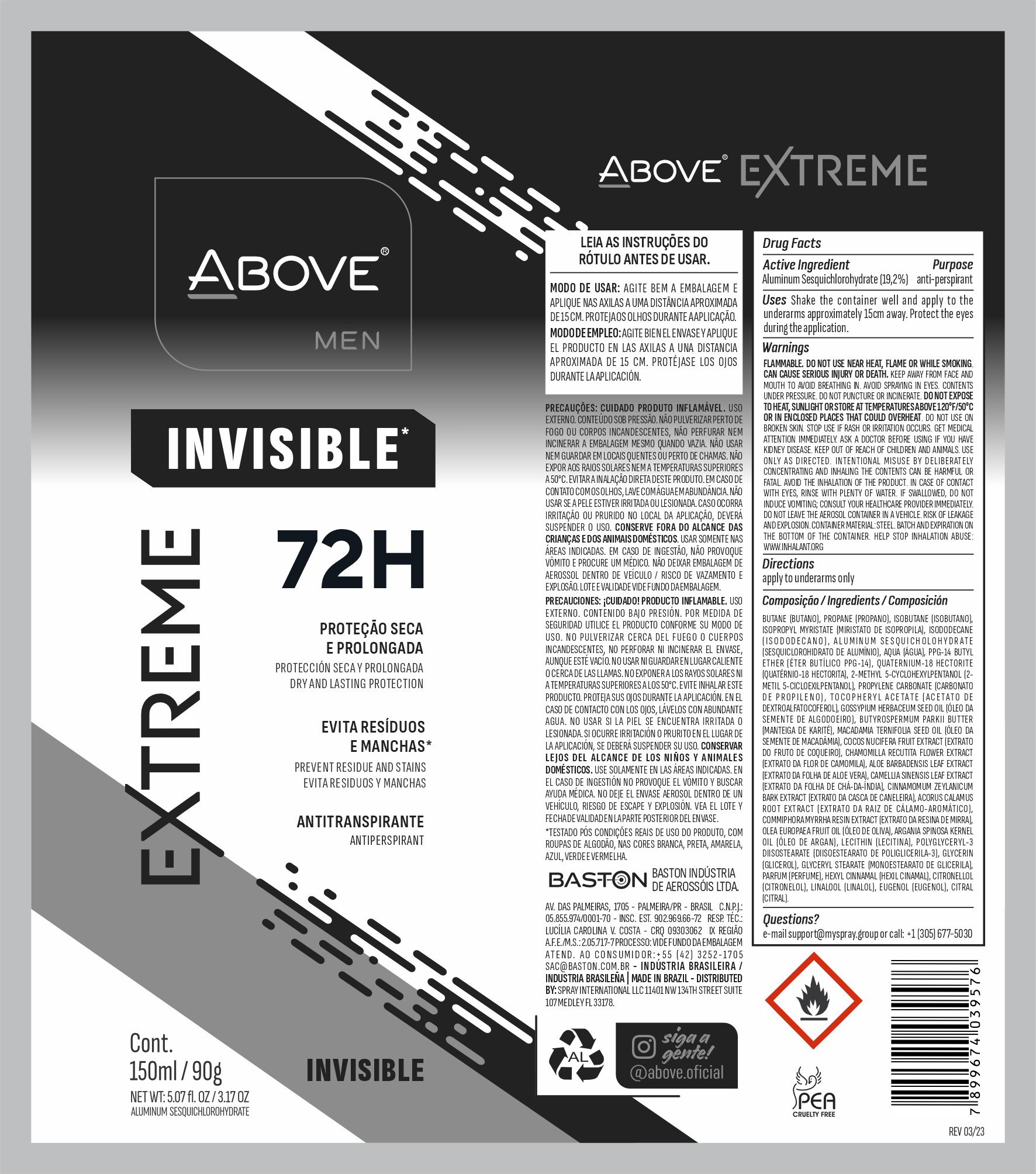 DRUG LABEL: ABOVE EXTREME INVISIBLE MEN 72 HOURS
NDC: 73306-1158 | Form: AEROSOL, SPRAY
Manufacturer: BASTON INDUSTRIA DE AEROSSOIS LTDA
Category: otc | Type: HUMAN OTC DRUG LABEL
Date: 20240709

ACTIVE INGREDIENTS: ALUMINUM SESQUICHLOROHYDRATE 19 mg/90 g
INACTIVE INGREDIENTS: ISOBUTANE

ABOVE EXTREME INVISIBLE MEN 72 HOURS SPRAY

ACTIVE INGREDIENT SECTION

ALUMINUM SESQUICHOLOHYDRATE

OTC PURPOSE SECTION

ANTIPERSPIRANT

Shake the container well and apply to the underarms approximately 15cm away. Protect the eyes during the application

Shake the container well and apply to the
underarms approximately 15cm away. Protect the eyes
during the application